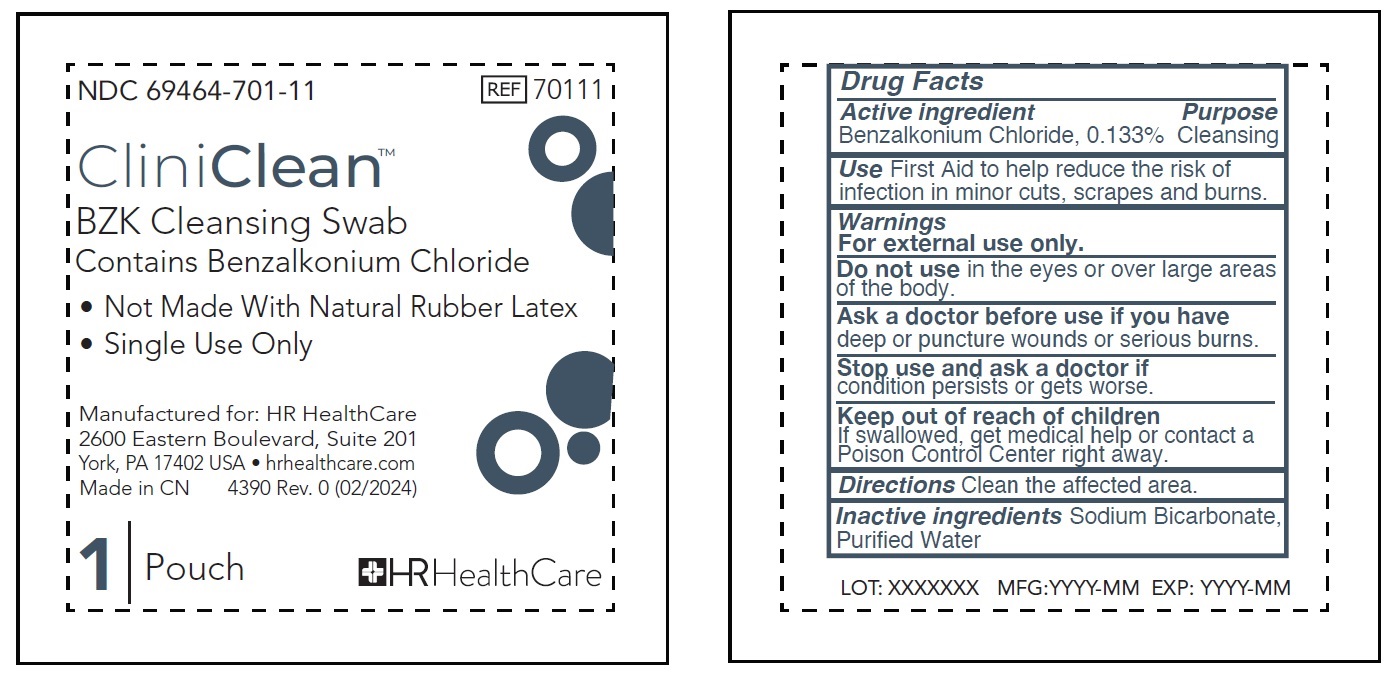 DRUG LABEL: CliniClean BZK Cleansing Contains Benzalkonium Chloride
NDC: 69464-701 | Form: LIQUID
Manufacturer: HR HealthCare
Category: otc | Type: HUMAN OTC DRUG LABEL
Date: 20240418

ACTIVE INGREDIENTS: BENZALKONIUM CHLORIDE 1.33 mg/1 g
INACTIVE INGREDIENTS: WATER

CliniClean BZK Cleansing Swab Contains Benzalkonium Chloride

Active ingredient

Benzalkonium Chloride, 0.133%

Purpose

Cleansing

Use

First Aid to help reduce the risk of infection in minor cuts, scrapes and burns.

Warnings

For external use only.

Do not use

in the eyes or over large areas of the body.

Ask a doctor before use if

you have deep or puncture wounds or serious burns.

Stop use and ask a doctor if

condition persists or gets worse.

Keep out of reach of children

If swallowed, get medical help or contact a Poison Control Center right away.

Directions

Clean the affected area.

Inactive ingredients

Sodium Bicarbonate, Purified Water